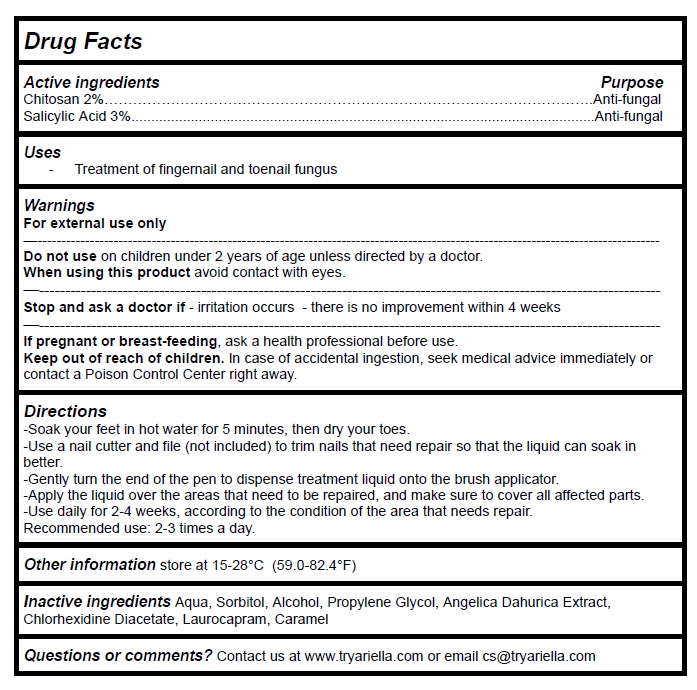 DRUG LABEL: Ariella Nail Repair Pen
NDC: 83364-001 | Form: LIQUID
Manufacturer: YITONGBADA (SHENZHEN) INTERNATIONAL TRADE CO., LTD
Category: otc | Type: HUMAN OTC DRUG LABEL
Date: 20230511

ACTIVE INGREDIENTS: POLIGLUSAM 2 g/100 mL; SALICYLIC ACID 3 g/100 mL
INACTIVE INGREDIENTS: WATER; SORBITOL; ALCOHOL; PROPYLENE GLYCOL; ANGELICA DAHURICA WHOLE; CHLORHEXIDINE ACETATE; LAUROCAPRAM; CARAMEL

Active Ingredient Purpose

Chitosan 2% Anti-fungal

Salicylic Acid 3% Anti-fungal

Uses

Treatment of fingernail and toenail fungus

Warnings

For external use only.

Do not use on children under 2 years of age unless directed by a doctor.

When using this product avoid contact with eyes.

Stop and ask a doctor if - irritation occurs - there is no improvement within 4 weeks

If pregnant or breast-feeding, ask a health professional before use.

Keep out of reach of children. In case of accidental ingestion, seek medical advice immediately or contact a Poison Control Center right away.

Directions

- Soak your feet in hot water for 5 minutes, then dry your toes.
- Use a nail cutter and file (not included) to trim nails that need repair so that the liquid can soak in better.
- Gently turn the end of the pen to dispense treatment liquid onto the brush applicator.
- Apply the liquid over the areas that need to be repaired, and make sure to cover all affected parts.
- Use daily for 2-4 weeks, according to the condition of the area that needs repair.
- Recommended use: 2-3 times a day.

Other information

store at 15-28°C (59.0-82.4°F)

Inactive ingredients

Aqua, Sorbitol, Alcohol, Propylene Glycol, Angelica Dahurica Extract,Chlorhexidine Diacetate, Laurocapram, Caramel

Questions or comments?

Contact us at www.tryariella.com or email cs@tryariella.com